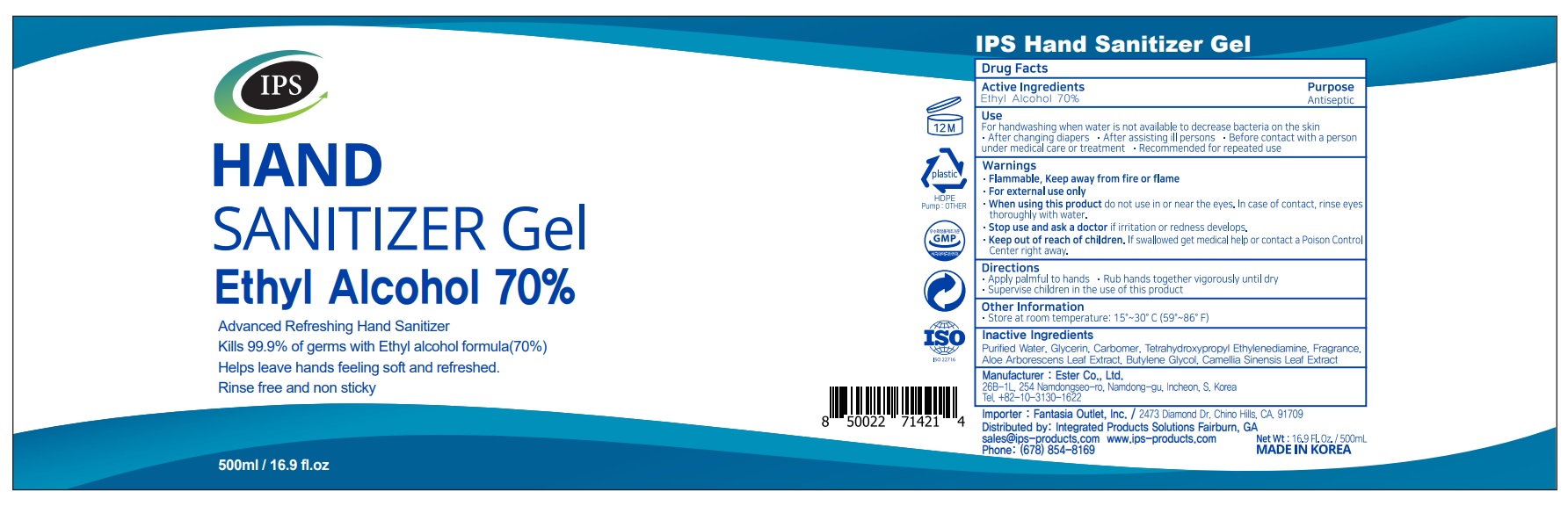 DRUG LABEL: IPS Hand Sanitizer Gel
NDC: 74004-750 | Form: GEL
Manufacturer: Ester Co., Ltd.
Category: otc | Type: HUMAN OTC DRUG LABEL
Date: 20200831

ACTIVE INGREDIENTS: ALCOHOL 350 mL/500 mL
INACTIVE INGREDIENTS: BUTYLENE GLYCOL; GREEN TEA LEAF; CARBOMER HOMOPOLYMER, UNSPECIFIED TYPE; WATER; EDETOL; GLYCERIN; ALOE ARBORESCENS LEAF

[Ester Co., Ltd.-IPS Hand Sanitizer Gel] 500 ml in Bottle+Pump : 74004-750-01